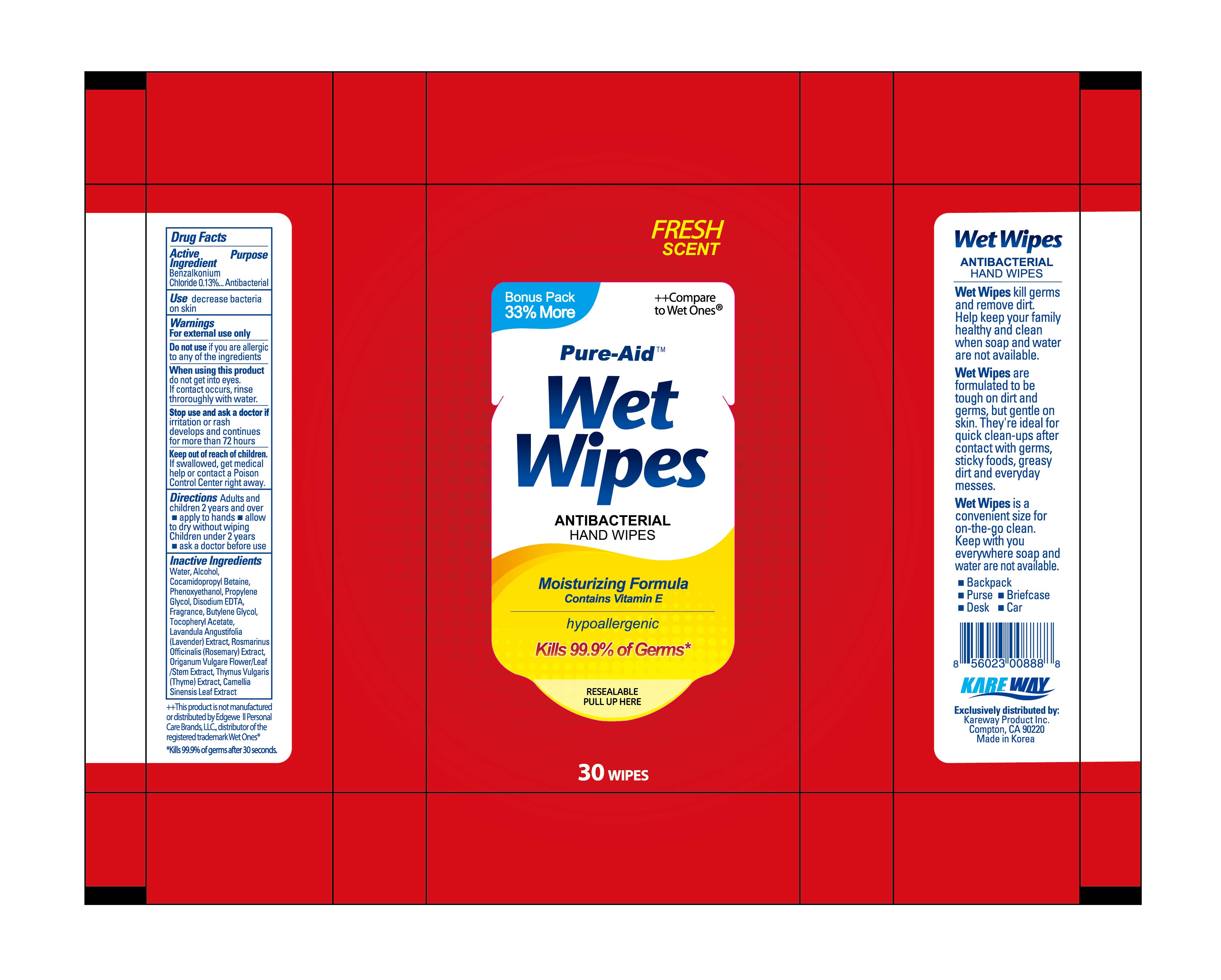 DRUG LABEL: Hand Wipes
NDC: 67510-1888 | Form: SWAB
Manufacturer: Kareway Product, Inc.
Category: otc | Type: HUMAN OTC DRUG LABEL
Date: 20200904

ACTIVE INGREDIENTS: BENZALKONIUM CHLORIDE 0.13 1/100 1
INACTIVE INGREDIENTS: GREEN TEA LEAF; WATER; ALCOHOL; BUTYLENE GLYCOL; COCAMIDOPROPYL BETAINE; PROPYLENE GLYCOL; ORIGANUM VULGARE SUBSP. HIRTUM FLOWER; EDETATE DISODIUM ANHYDROUS; .ALPHA.-TOCOPHEROL ACETATE; LAVANDULA ANGUSTIFOLIA FLOWERING TOP; ROSEMARY; PHENOXYETHANOL; THYME

Pure-Aid Hand Wipes

Active Ingredients

Benzalkonium Chloride 0.13%

Purpose

Antibacterial

Use

decrease bacteria on skin

Warnings

For external use only

Do not use

if you are allergic to any of the ingredients

When using this product

do not get into eyes. If contact occurs, rinse throroughly with water.

Stop use and ask a doctor

if irritation or rash develops and continues for more than 72 hours

Keep out of reach of children

If swallowed, get medical help or contact a Poison Control Center right away.

Directions

adults and children 2 years and over

- apply to hands
- allow to dry without wiping

Children under 2 years

- ask a doctor before use

Inactive Ingredients

Water, Alcohol, Cocamidopropyl Betaine, Phenoxyethanol, Propylene Glycol, Disodium EDTA, Fragrance, Butylene Glycol, Tocopheryl Acetate, Lavandula Angustifolia (Lavender) Extract, Rosmarinus Officinalis (Rosemary) Extract, Origanum Vulgare Flower/Leaf/Stem Extract, Thymus Vulgaris (Thyme) Extract, Camellia Sinensis Leaf Extract

Principle Display Panel

Fresh Scent

Wet wiptes

Antibacterial formula

30 wipes